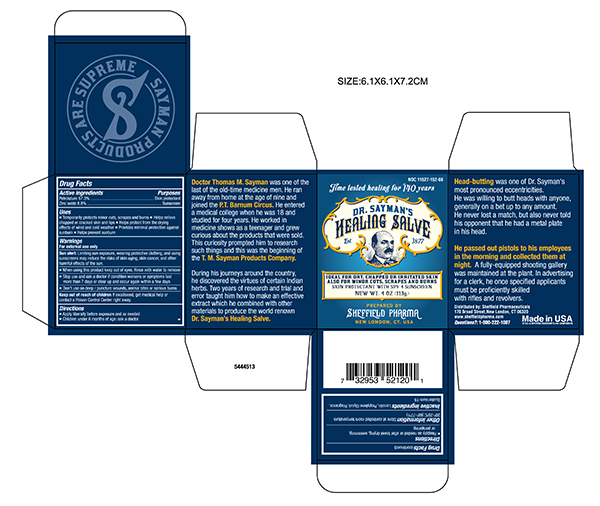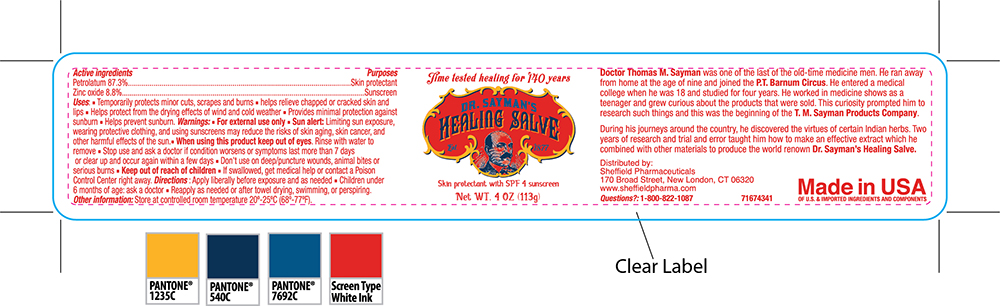 DRUG LABEL: Dr. Sayman Salve
NDC: 11527-152 | Form: OINTMENT
Manufacturer: Sheffield Pharmaceuticals LLC
Category: otc | Type: HUMAN OTC DRUG LABEL
Date: 20231024

ACTIVE INGREDIENTS: PETROLATUM 87.3 mg/1 g; ZINC OXIDE 8.8 mg/1 g
INACTIVE INGREDIENTS: LANOLIN; PROPYLENE GLYCOL; QUATERNIUM-15

Dr Sayman Salve

Active ingredient

Petrolatum - 87.3 %

Zinc Oxide- 8.8%

Purpose

Skin protectant

Sunscreen

Uses

- Temporarily protects minor cuts,scrapes and burns.
- Helps releive chapped or cracked skin and lips.
- Helps protectfrom the drying effects of windand cold weather.
- Providesminimalportection agaisnt sunburn.
- Helps prevent sunburn.

Warnings

For external use only

Sun Alert: limiting sun exposure,wearing protectvie clothing,and usingsunscreens may reduce the risks of skin aging, skin cancer, and other harmful effects of the sun.

- When using this product keep out of eyes. Rinse with water to remove.
- Stop use and ask a doctor if condition worsens or symptoms last more than seven days or clear up and occur again within a few days.
- Don't use on deep/ puncture wounds,animal bites or serious burns.

Directions

- Apply liberally before exposureand as needed
- Children under 6 months of age:ask a doctor
- Reapply as needed or after towel drying,swimming

Other information

Store at controlled room temperature 20°C -25°C (68°F - 77°F)

Inactive ingredients

Lanolin, Propylene Glycol, Fragrance, Quaternium-15

Principal Display Panel -Jar

Dr Sayman's Salve NDC 11527-152-68

Healing Salve

Ideal for Dry, Chapped or Irritated skin

Also for minor cut,scrapes and burns

NET WT 4 oz (113g)

Principal Display Panel -Carton

Dr Sayman's Salve NDC 11527-152-68

Healing Salve

Ideal for Dry, Chapped or Irritated Skin

Also for minor cuts, scapes and burns

NET WT 4 oz (113g)